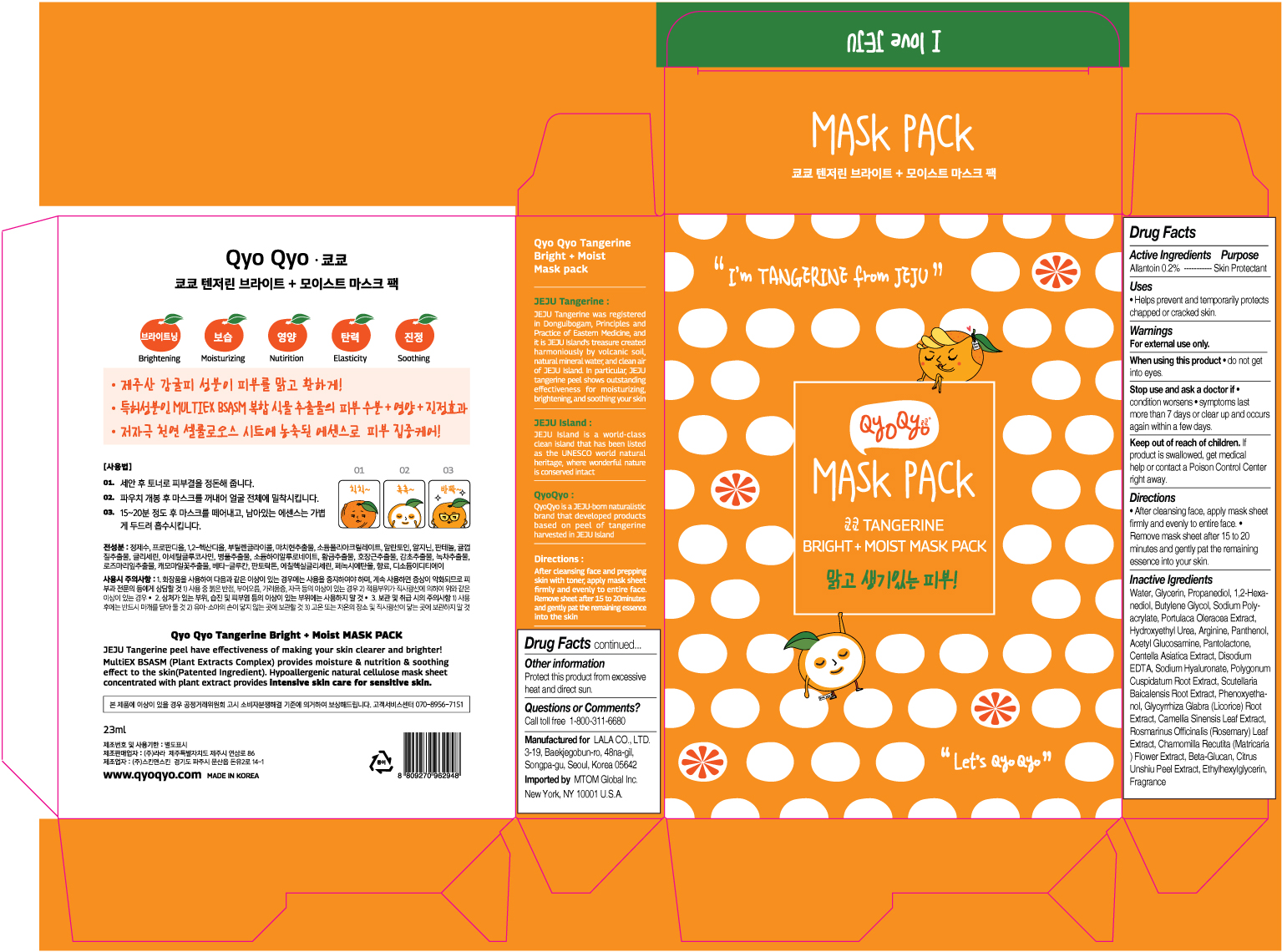 DRUG LABEL: QYO QYO Tangerine Bright Moist Mask Pack
NDC: 71733-106 | Form: CLOTH
Manufacturer: LaLa Co., Ltd.
Category: otc | Type: HUMAN OTC DRUG LABEL
Date: 20190101

ACTIVE INGREDIENTS: ALLANTOIN 0.2 g/23 mL
INACTIVE INGREDIENTS: BUTYLENE GLYCOL; TANGERINE PEEL; WATER; GLYCERIN; 1,2-HEXANEDIOL

Qyo Qyo Tangerine Bright + Moist Mask Pack

ACTIVE INGREDIENTS

ALLANTOIN 0.2%

PURPOSE

SKIN PROTECTANT

USES

- Helps prevent and temporarily protects chapped or cracked skin.

WARNINGS

For external use only.

When using this product • do not get into eyes.

STOP USE

Stop us and ask doctor if • condition worsens • symptoms last
more than 7 days or clear up and occurs again within a few days.

Keep out of reach of children. If product is swallowed, get medical help or contact a Poison Control Center right away.

Directions

• After cleansing face, apply mask sheet firmly and evenly to entire face.
• Remove mask sheet after 15 to 20 minutes and gently pat the remaining essence into your skin.

Inactive Ingredients

Water, Glycerin, Propanediol, 1,2-Hexanediol, Butylene Glycol, Sodium Polyacrylate, Portulaca Oleracea Extract, Hydroxyethyl Urea, Arginine, Panthenol, Acetyl Glucosamine, Pantolactone, Centella Asiatica Extract, Disodium EDTA, Sodium Hyaluronate, Polygonum Cuspidatum Root Extract, Scutellaria Baicalensis Root Extract, Phenoxyethanol, Glycyrrhiza Glabra (Licorice) Root Extract, Camellia Sinensis Leaf Extract, Rosmarinus Officinalis (Rosemary) Leaf Extract, Chamomilla Recutita (Matricaria) Flower Extract, Beta-Glucan, Citrus Unshiu Peel Extract, Ethylhexylglycerin, Fragrance

Other Information

Protect this product from excessive heat and direct sun.

Questions or Comments?

Call toll free 1-800-311-6680